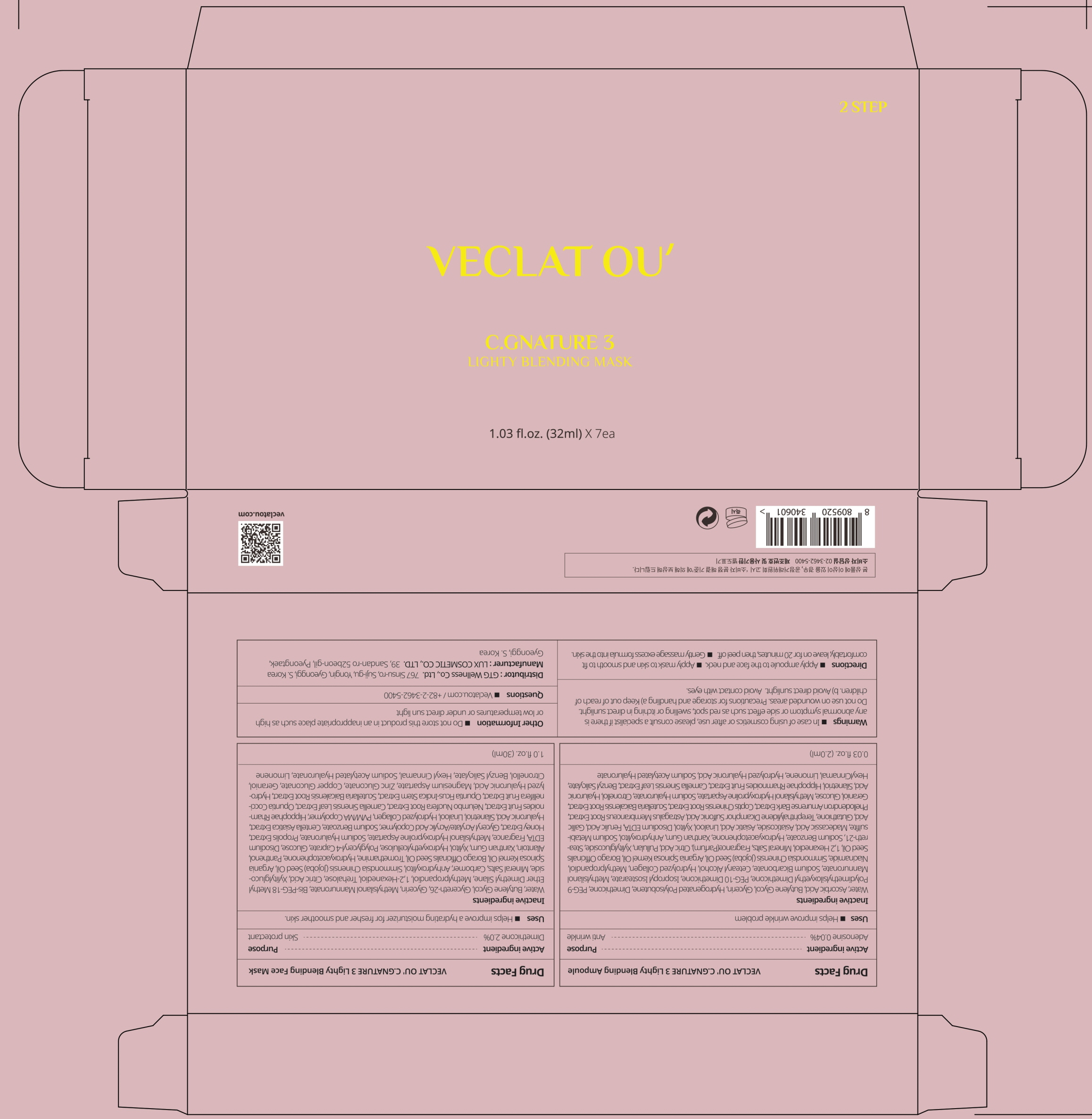 DRUG LABEL: VECLAT OU C.GNATURE 3 Lighty Blending Face Mask
NDC: 71080-0025 | Form: PATCH
Manufacturer: GTG WELLNESS CO., LTD.
Category: otc | Type: HUMAN OTC DRUG LABEL
Date: 20211124

ACTIVE INGREDIENTS: Dimethicone 2.0 g/100 mL
INACTIVE INGREDIENTS: Water; Butylene Glycol; Glycereth-26; Glycerin

ACTIVE INGREDIENT

Dimethicone 2.0%

INACTIVE INGREDIENTS

Water, Butylene Glycol, Glycereth-26, Glycerin, Methylsilanol Mannuronate, Bis-PEG-18 Methyl Ether Dimethyl Silane, Methylpropandiol, 1,2-Hexanediol, Trehalose, Citric Acid, Xylitylglucoside, Mineral Salts, Carbomer, Anhydroxylitol, Simmondsia Chinensis (Jojoba) Seed Oil, Argania Spinosa Kernel Oil, Borago Officinalis Seed Oil, Tromethamine, Hydroxyacetophenone, Panthenol, Allantoin, Xanthan Gum, Xylitol, Hydroxyethylcellulose, Polyglyceryl-4 Caprate, Glucose, Disodium EDTA, Fragrance, Methylsilanol Hydroxyproline Aspartate, Sodium Hyaluronate, Propolis Extract, Honey Extract, Glyceryl Acrylate/Acrylic Acid Copolymer, Sodium Benzoate, Centella Asiatica Extract, Hyaluronic Acid, Silanetriol, Linalool, Hydrolyzed Collagen, PVM/MA Copolymer, Hippophae Rhamnoides Fruit Extract, Nelumbo Nucifera Root Extract, Camellia Sinensis Leaf Extract, Opuntia Coccinellifera Fruit Extract, Opuntia Ficus-Indica Stem Extract, Scutellaria Baicalensis Root Extract, Hydrolyzed Hyaluronic Acid, Magnesium Aspartate, Zinc Gluconate, Copper Gluconate, Geraniol, Citronellol, Benzyl Salicylate, Hexyl Cinnamal, Sodium Acetylated Hyaluronate, Limonene

PURPOSE

Skin protectant

WARNINGS

In case of using cosmetics or after use, please consult a specialist if there is any abnormal symptom or side effect such as red spot, swelling or itching in direct sunlight.
Do not use on wounded areas.
Precautions for storage and handling
a) Keep out of reach of children.
b) Avoid direct sunlight.
Avoid contact with eyes.

KEEP OUT OF REACH OF CHILDREN

Uses

■ Helps improve a hydrating moisturizer for fresher and smoother skin.

Directions

■ Apply ampoule to the face and neck.
■ Apply mask to skin and smooth to fit comfortably, leave on for 20 minutes, then peel off.
■ Gently massage excess formula into the skin.

Other information

■ Do not store this product in an inappropriate place such as high or low temperatures or under direct sun light

Questions

■ Veclatou.com / +82-2-3462-5400